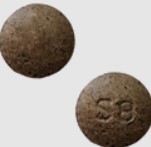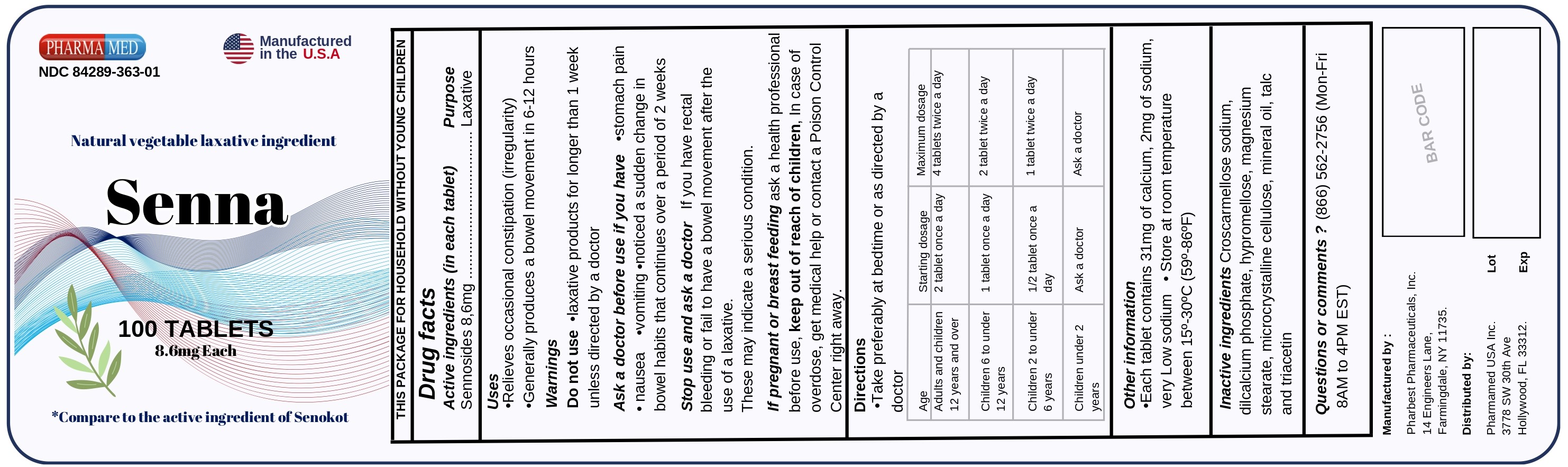 DRUG LABEL: Senna-Tabs
NDC: 84289-363 | Form: TABLET, FILM COATED
Manufacturer: PHARMAMED USA INC
Category: otc | Type: HUMAN OTC DRUG LABEL
Date: 20240627

ACTIVE INGREDIENTS: SENNOSIDES 8.6 mg/1 1
INACTIVE INGREDIENTS: CELLULOSE, MICROCRYSTALLINE; MINERAL OIL; MAGNESIUM STEARATE; CALCIUM PHOSPHATE, DIBASIC, ANHYDROUS; HYPROMELLOSE, UNSPECIFIED; TRIACETIN; CROSCARMELLOSE SODIUM; TALC

Senna 8.6mg Tablets

Active ingredient (in each tablet)

Sennosides 8.6mg

Purpose

Laxative

Uses

- relieves occasional constipation (irregularity)
- generally produces a bowel movement in 6-12 hours

Warnings

Do not use

- laxative products for longer than 1 week unless directed by a doctor

Ask a doctor before use if you have

- stomach pain
- nausea
- vomiting
- noticed a sudden change in bowel habits that continues over a period of 2 weeks

Stop use and ask a doctor if

you have rectal bleeding or fail to have a bowel movement after the use of a laxative.

These may indicate a serious condition.

If pregnant or breast feeding,

ask a health professional before use.

Keep out of reach of children.

In case of an overdose, get medical help or contact a Poison Control Center right away (1 800-222-1222).

Directions

- take preferably at bedtime or as directed by a doctor

age | starting dosage | maximum dosage
adults and children 12 years and over | 2 tablets once a day | 4 tablets twice a day
children 6 to under 12 years | 1 tablet once a day | 2 tablets twice a day
children 2 to under 6 years | ½ tablet once a day | 1 tablet twice a day
children under 2 years | ask a doctor | ask a doctor

Other information

- each tablet contains: calcium 31 mg, sodium 2 mg, Very Low Sodium
- store at 20º -25ºC (68º-77ºF); excursions permitted between 15º -30º C (59º-86º F)

Inactive ingredients

croscarmellose sodium, dicalcium phosphate, hypromellose, magnesium stearate, microcrystalline cellulose, mineral oil, talc, triacetin

Questions or comments?

(866) 562-2756 (Mon - Fri 8 AM to 4 PM EST)

Package Label Principal Display Panel

PHARMAMED

NDC 84289-363-01

Manufactured in the USA

Natural Vegetable Laxative Ingredient

Senna

100 TABLETS

8.6 mg each

*Compare to the active ingredient of Senokot